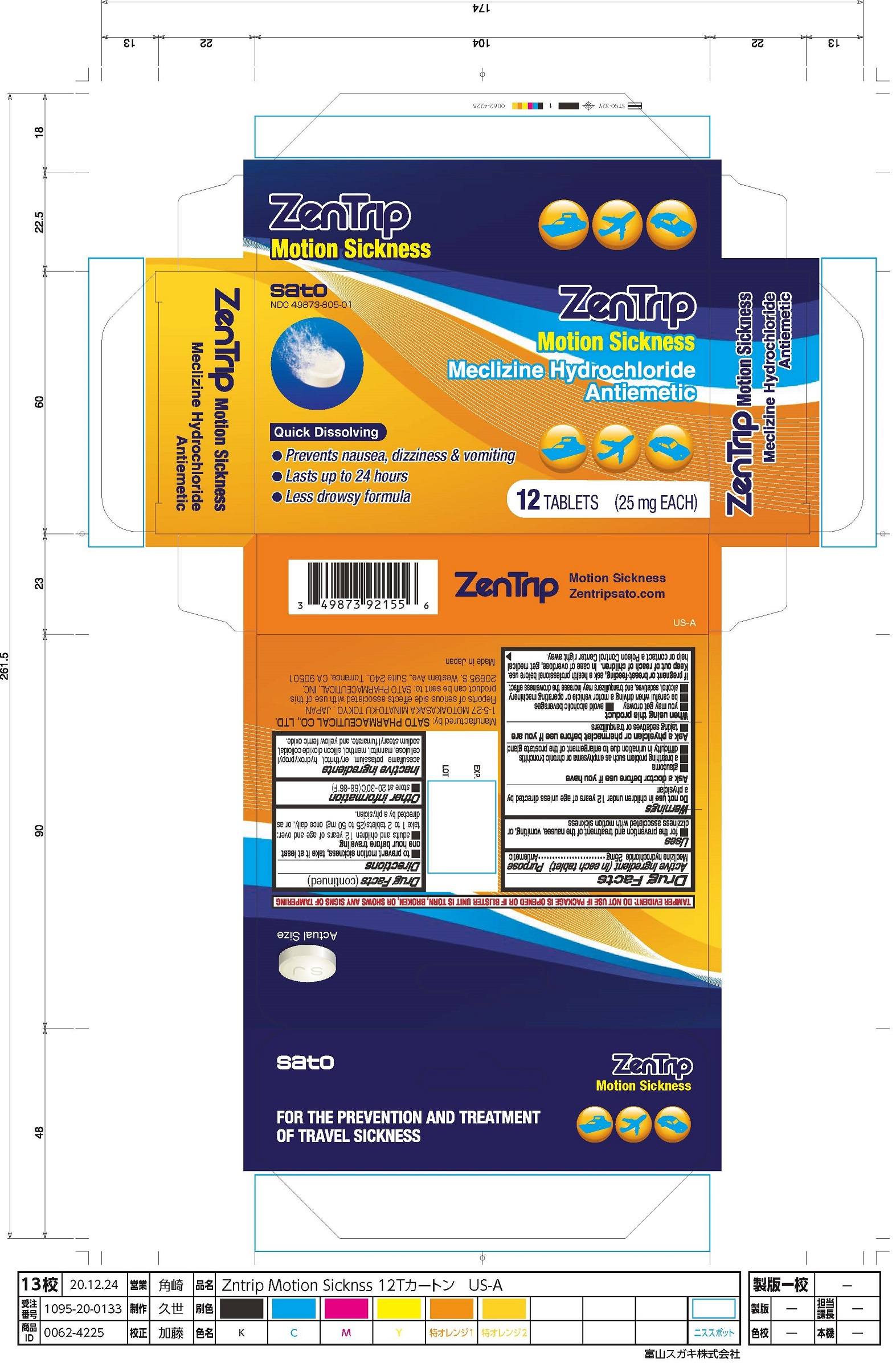 DRUG LABEL: ZenTrip Motion Sickness
NDC: 49873-805 | Form: TABLET
Manufacturer: Sato Pharmaceutical Co., LTD
Category: otc | Type: HUMAN OTC DRUG LABEL
Date: 20231103

ACTIVE INGREDIENTS: MECLIZINE HYDROCHLORIDE 25 mg/1 1
INACTIVE INGREDIENTS: ACESULFAME POTASSIUM; MANNITOL; MENTHOL; FERRIC OXIDE YELLOW; ERYTHRITOL; SILICON DIOXIDE; SODIUM STEARYL FUMARATE; HYDROXYPROPYL CELLULOSE (1600000 WAMW)

ZenTrip Motion Sickness (12 Tablets - 25mg each)

Active ingredient (in each tablet)

Meclizine hydrochloride 25mg

Purpose

Antiemetic

Uses

- for the prevention and treatment of the nausea, vomiting, or dizziness associated with motion sickness

Warnings

Do not use in children under 12 years of age unless directed by a physician

Ask a doctor before use if you have

- glaucoma
- a breathing problem such as emphysema or chronic bronchitis
- difficulty in urination due to enlargement of the prostate gland

Ask a physician or pharmacist before use if you are

- taking sedatives or tranquilizers

When using this product

- you may get drowsy
- be careful when driving a motor vehicle or operating machinery
- alcohol, sedatives, and tranquilizers may increase the drowsiness effect
- avoid alcoholic beverages

If pregnant or breast-feeding,

ask a health professional before use.

Keep out of reach of children.

In case of overdose, get medical help or contact a Poison Control Center right away.

Directions

- to prevent motion sickness, take it at least one hour before traveling
- adults and children 12 years of age and over: take 1 to 2 tablets (25 to 50mg) once daily, or as directed by a physician.

Other information

- store at 20-30°C (68-86°F)

Inactive ingredients

acesulfame potassium, erythritol, hydroxypropyl cellulose, mannitol, menthol, silicon dioxide colloidal, sodium stearyl fumarate, and yellow ferric oxide.